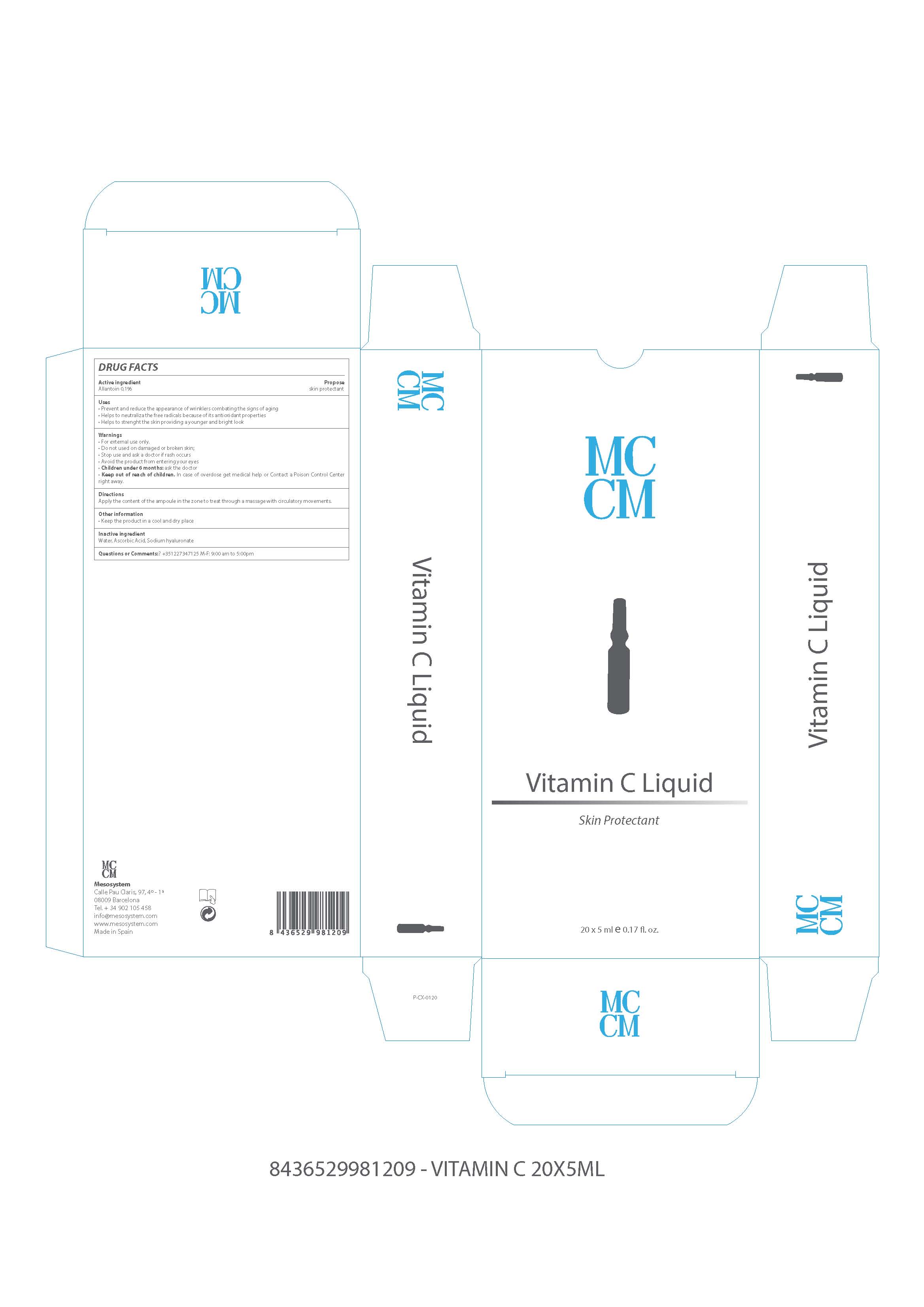 DRUG LABEL: Vitamin C Liquid
NDC: 70663-004 | Form: LIQUID
Manufacturer: MESO SYSTEM S A
Category: otc | Type: HUMAN OTC DRUG LABEL
Date: 20171102

ACTIVE INGREDIENTS: ALLANTOIN 0.1 mg/1 mL
INACTIVE INGREDIENTS: HYALURONATE SODIUM 12 mg/1 mL; ASCORBIC ACID 20 mg/1 mL; WATER 67.9 mg/1 mL

VITAMIN C LIQUID

INACTIVE INGREDIENT

water, ascorbic acid, hyaluronate sodium

Warnings

Stop use and ask a Doctor if

- Conditions worsens
- Symptons last more than 7 days or clear up and occur again within a few days

WARNINGS

For external use only. When using this product:

- Do not get into eyes

Stop use and ask a Doctor if

- Conditions worsens
- Symptons last more than 7 days or clear up and occur again within a few days

USES

For its antioxidants properties helps to neutralize the free radicals, protecting the skin. It helps to prevent and reduce the appearance of wrinklers, combating the signs of ageing. It is used as coadjuvant in the production of collagen and helps to strenghten the skin, providing a younger and brighter look

USES

For its antioxidants properties helps to neutralize the free radicals, protecting the skin. It helps to prevent and reduce the appearance of wrinklers, combating the signs of ageing. It is used as coadjuvant in the production of collagen and helps to strenghten the skin, providing a younger and brighter look

Keep out of reach of babies and childrens

DIRECTIONS

Apply the content of the ampoule in the zone to treat through a massage with circulatory movements

QUESTIONS OR COMMENTS?

+35 1227347125 M-F: 9:00 am to 5:00 pm

ACTIVE INGREDIENT

ACTIVE INGREDIENT PURPOSE

Allantoin..............................................................Skin Protectant

VITAMIN C LIQUID

Skin Protectant